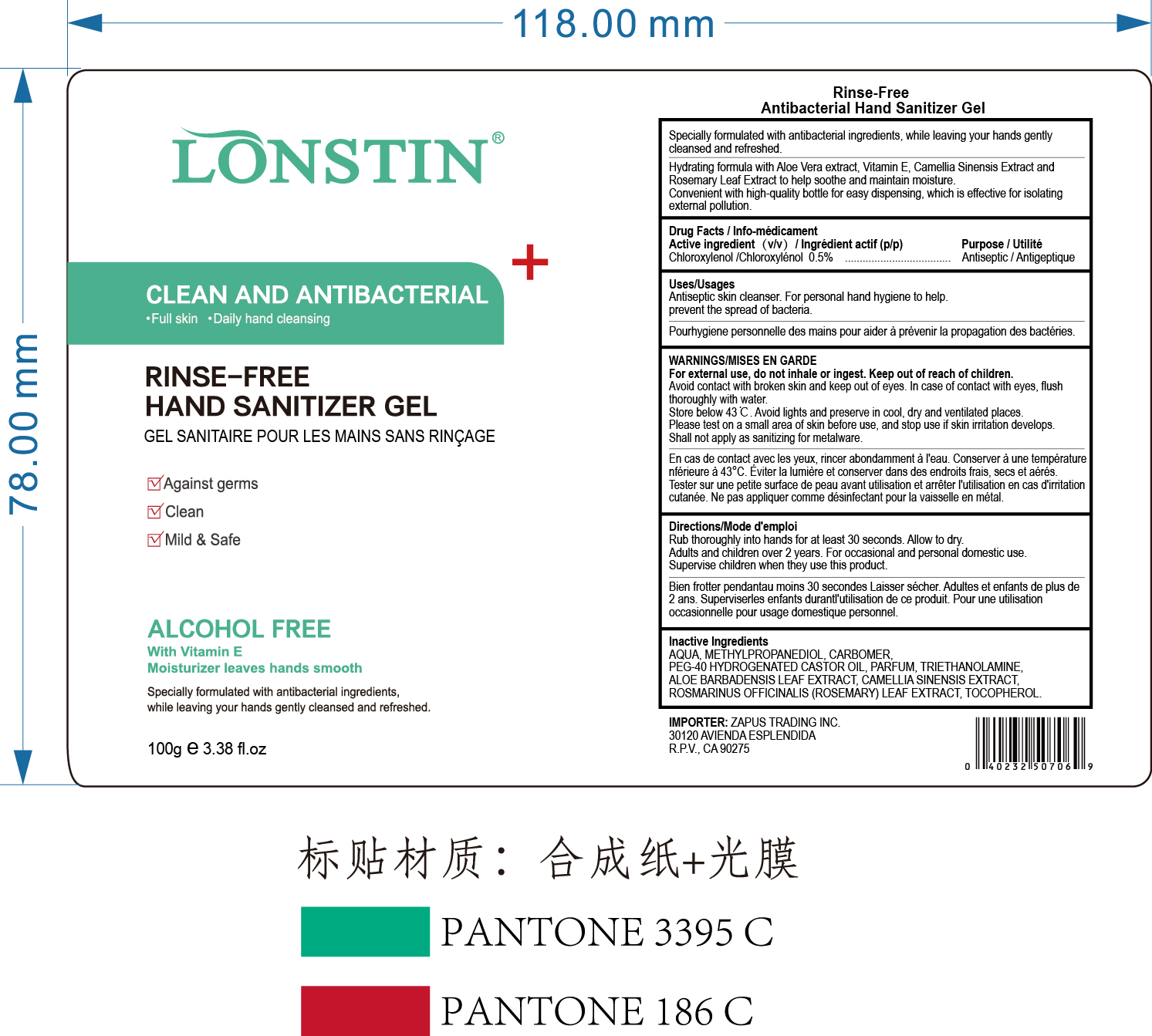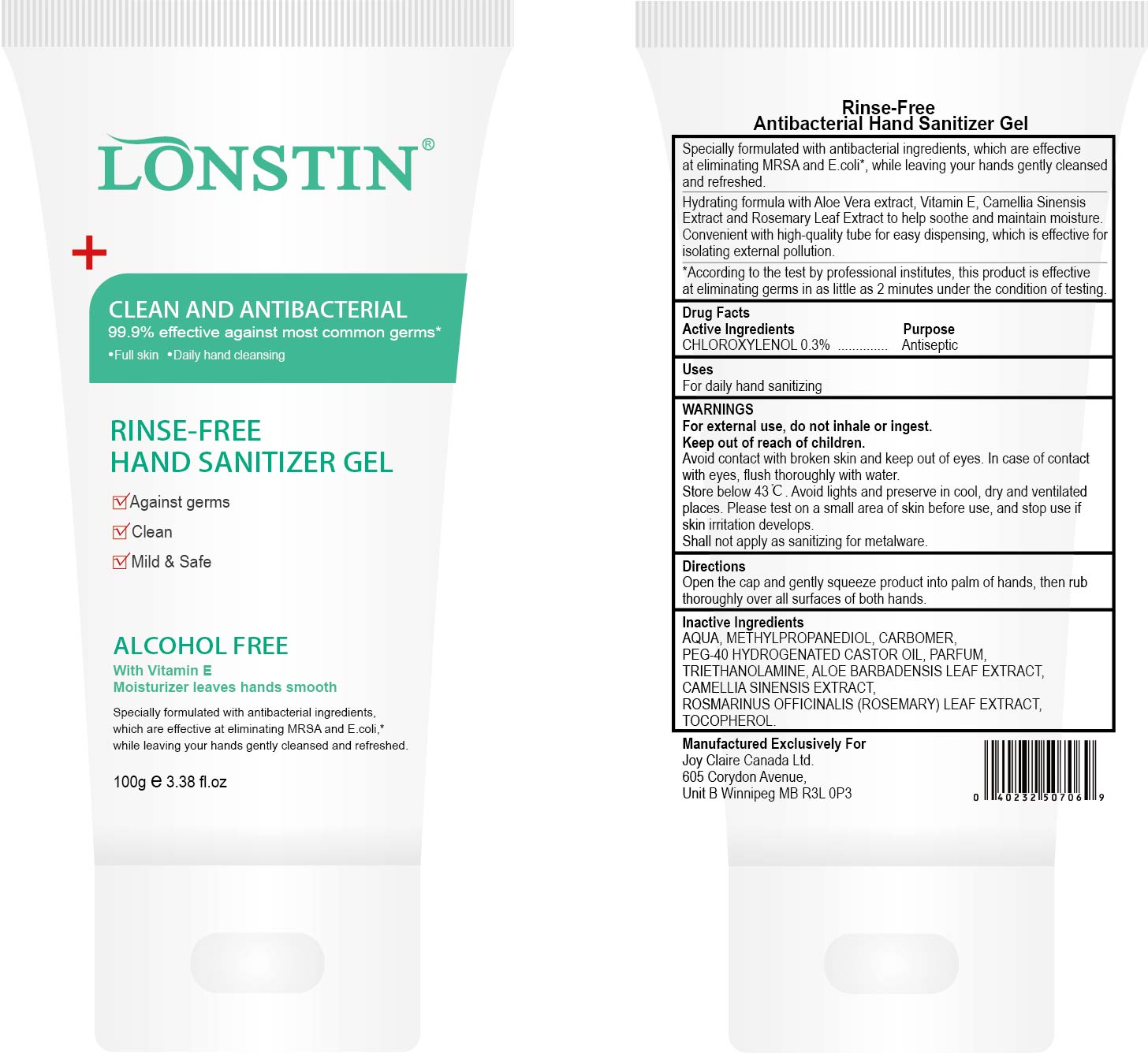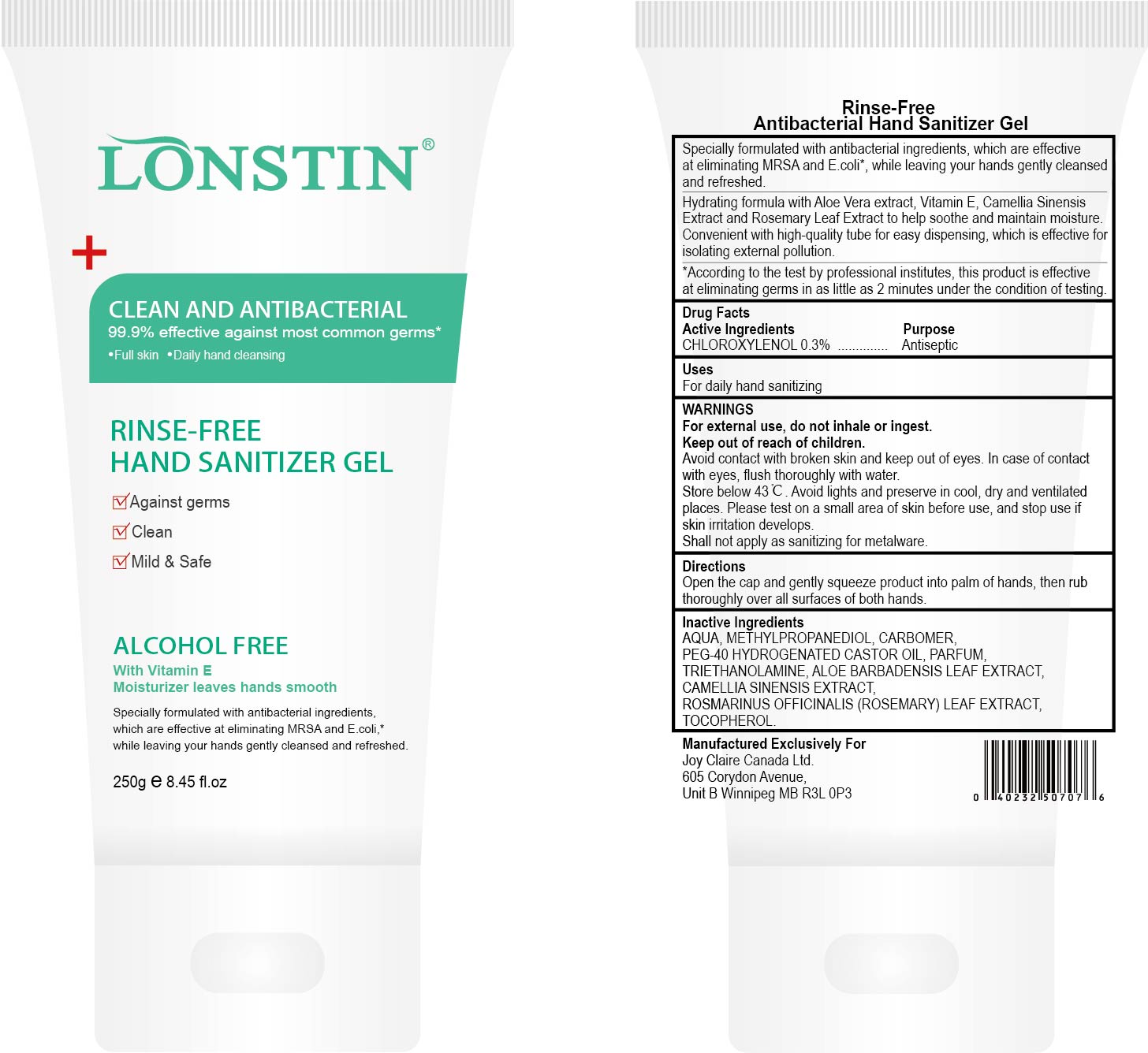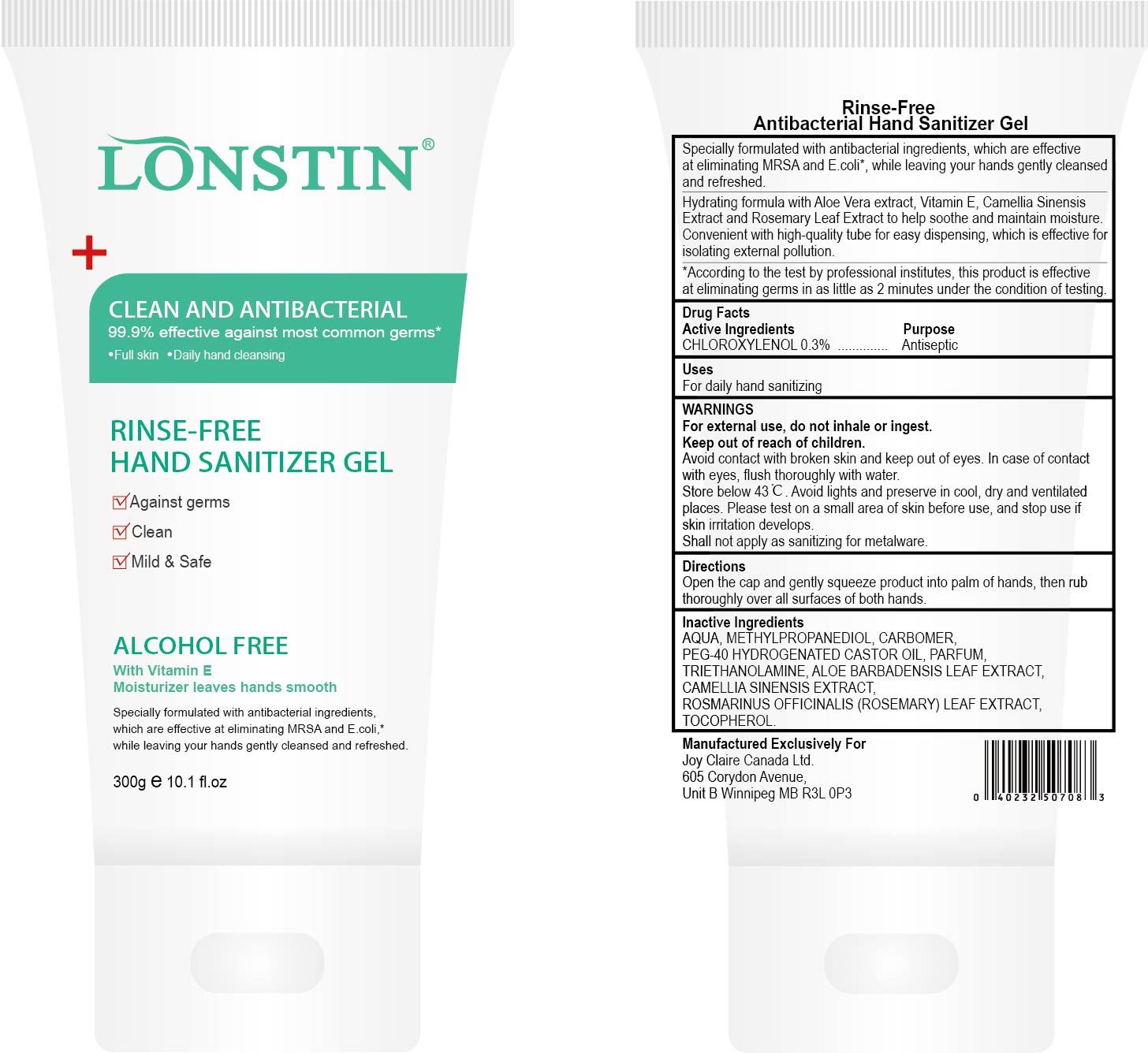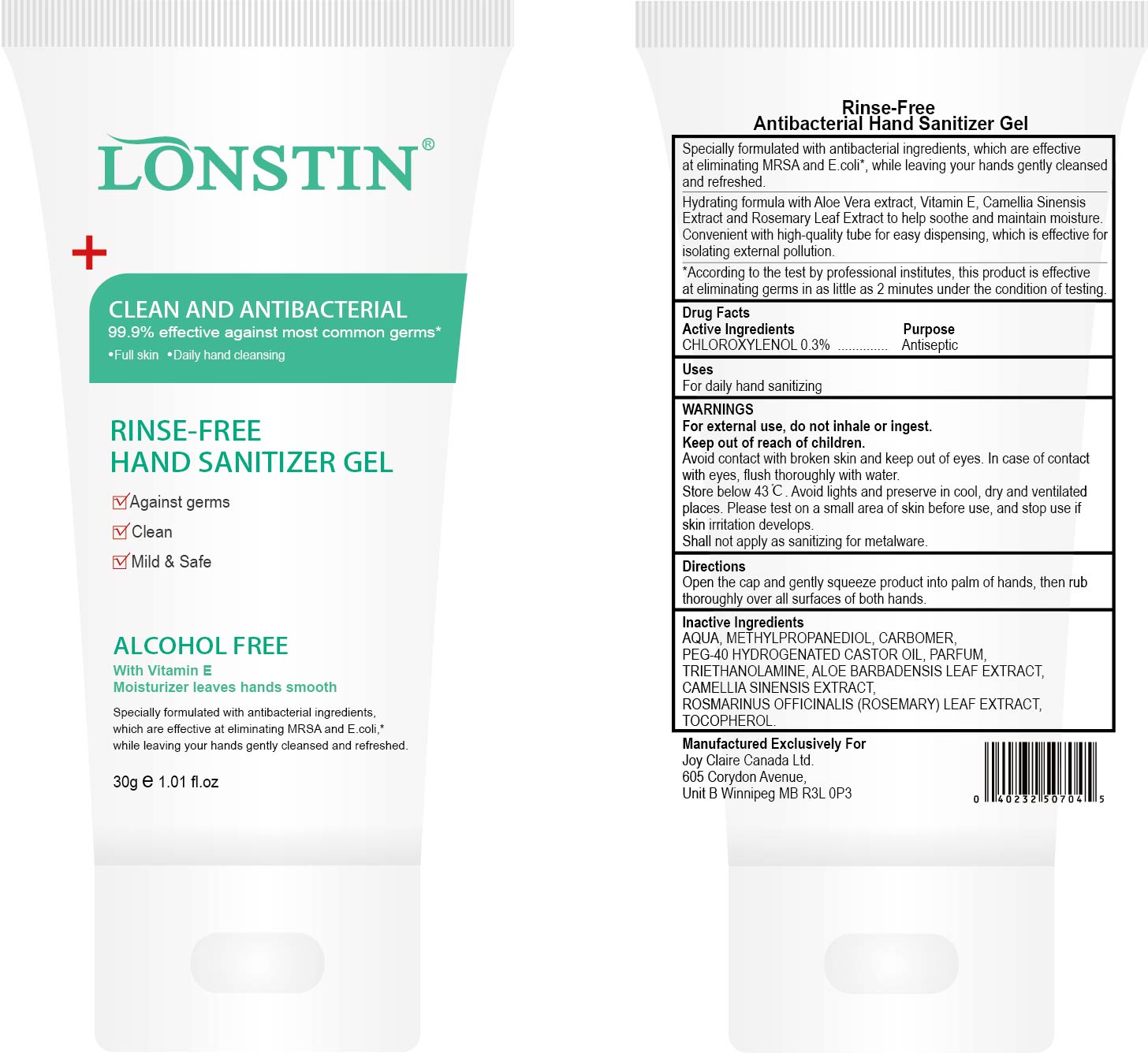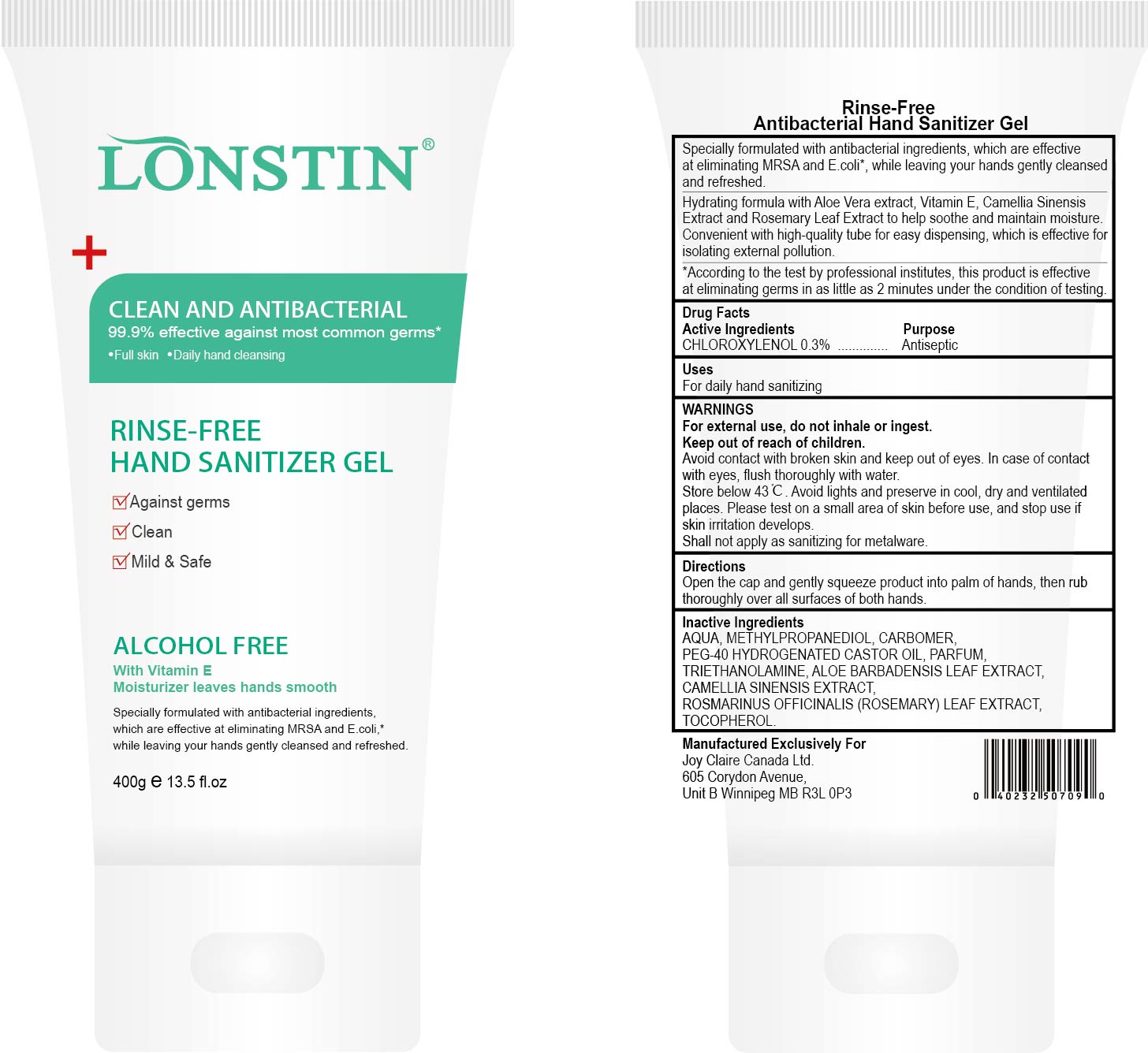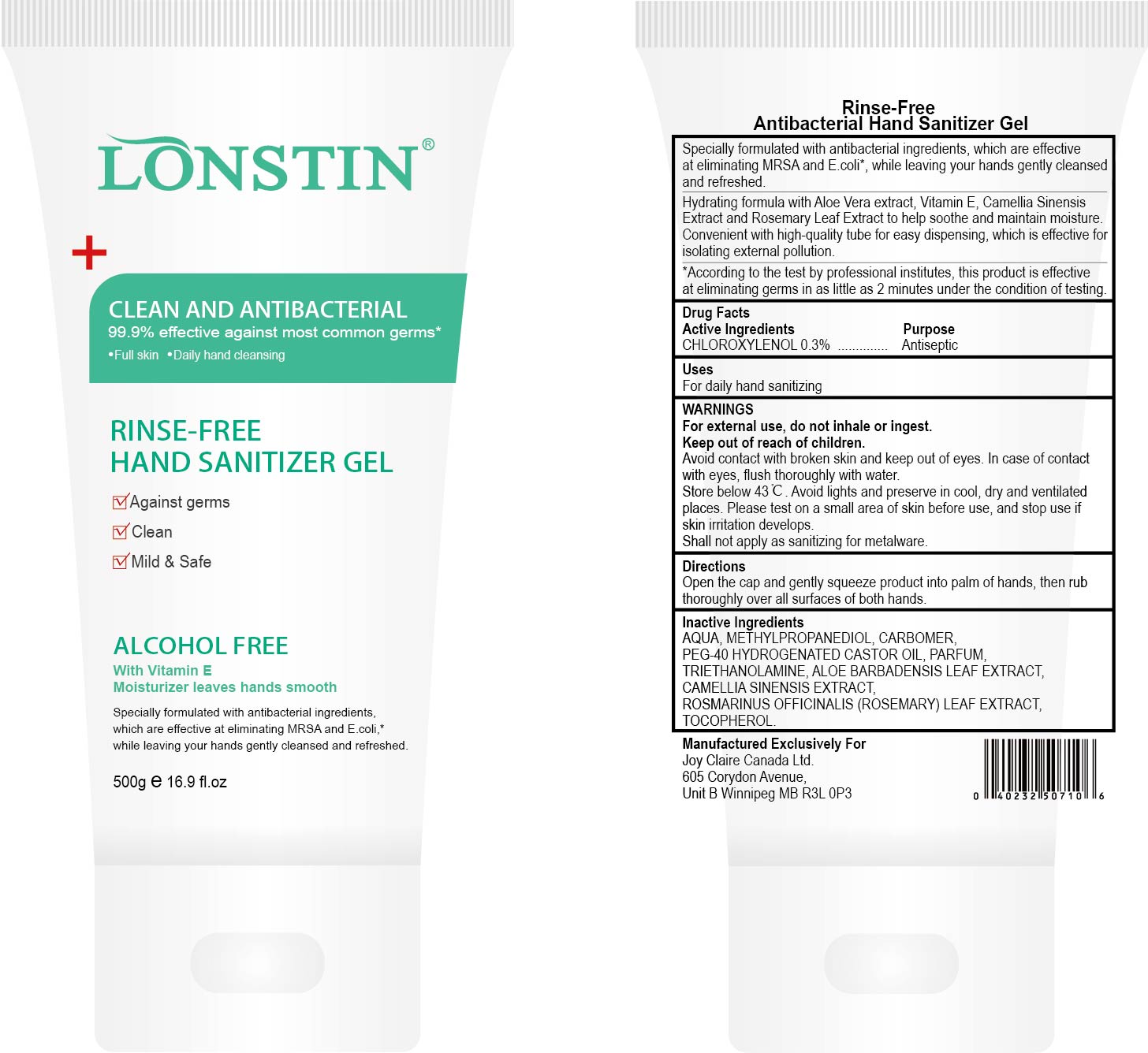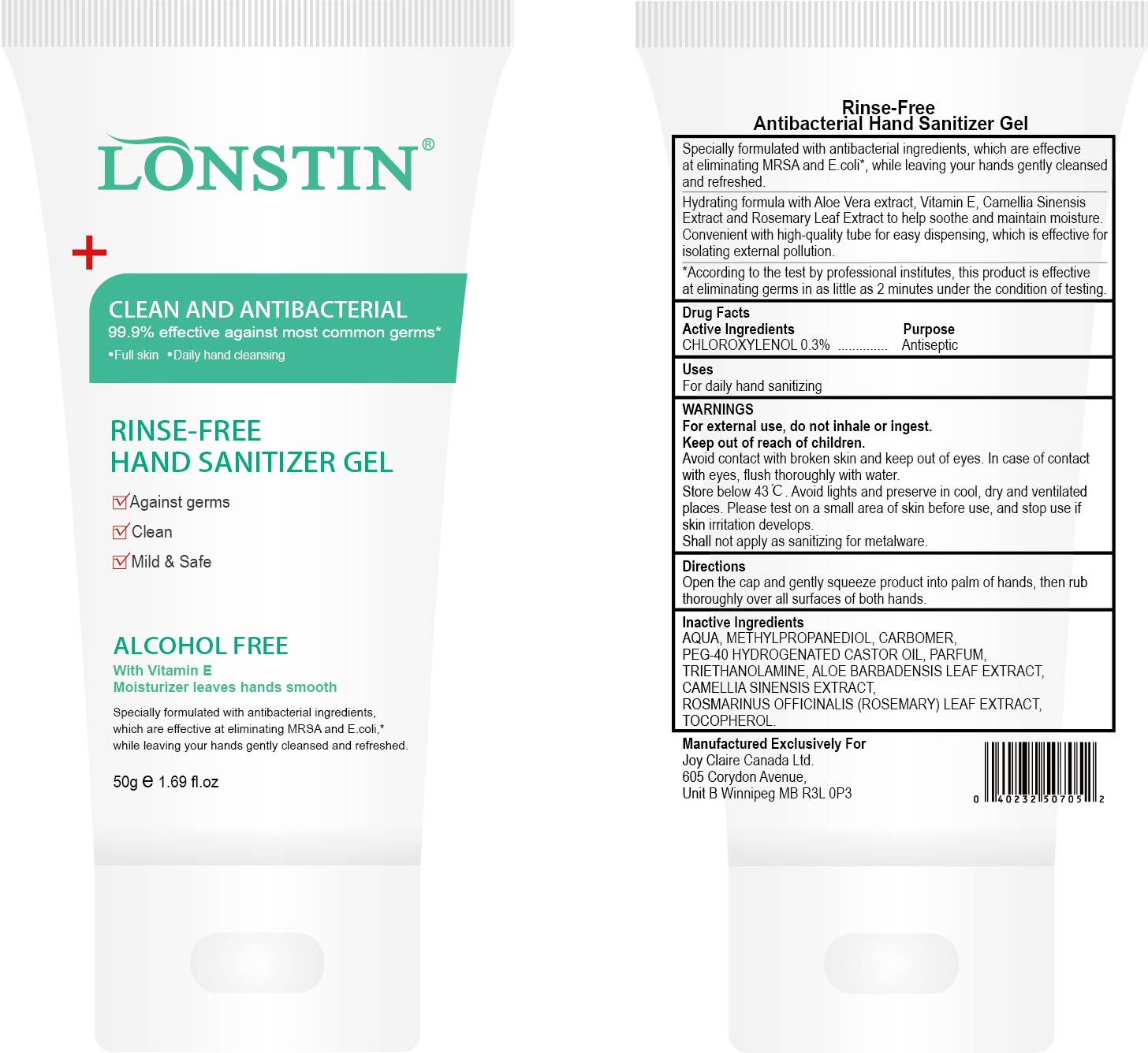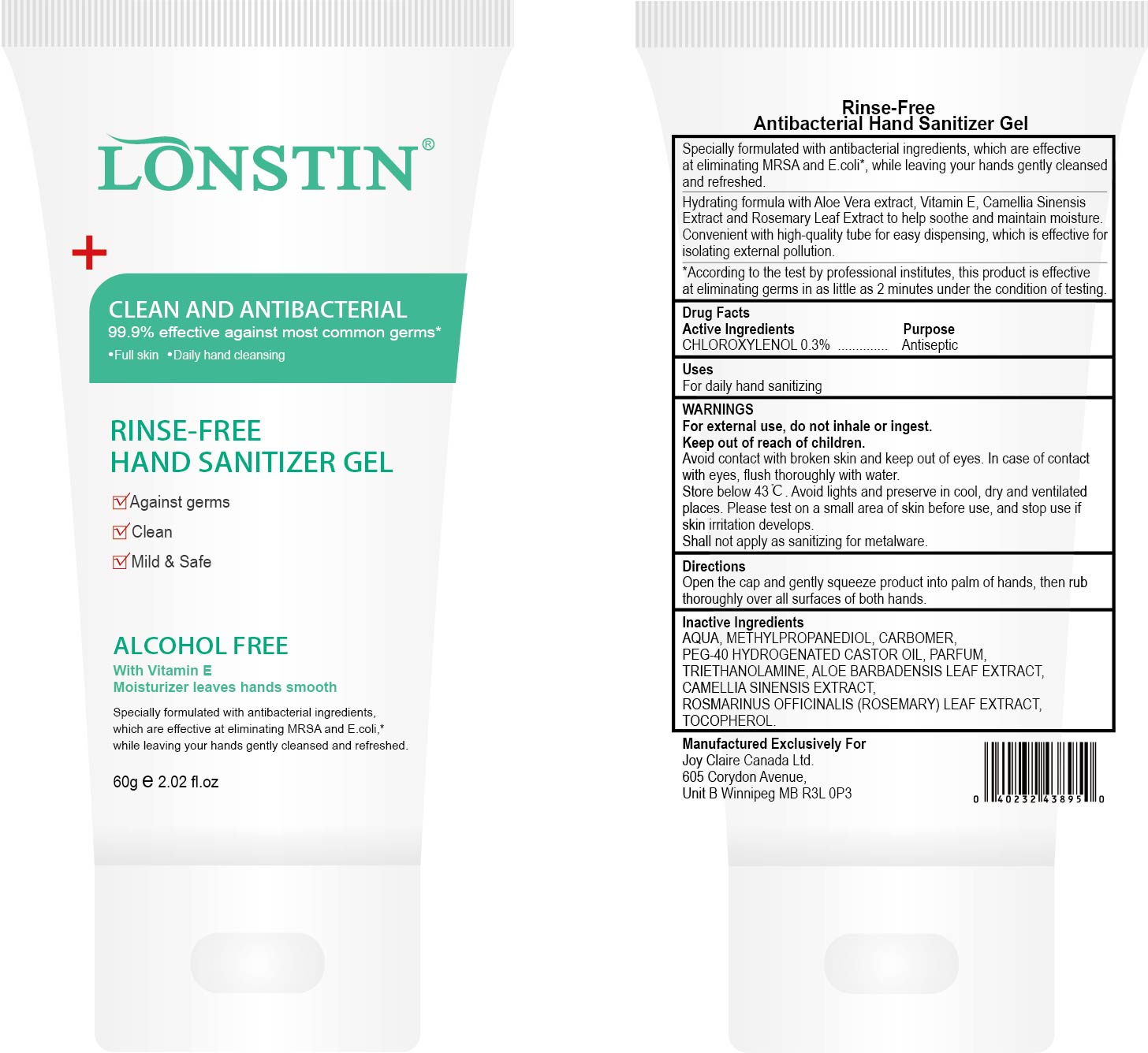 DRUG LABEL: Rinse-Free Hand Sanitizer
NDC: 74743-005 | Form: GEL
Manufacturer: Guangzhou Joy Claire Biological Technology   Co., Ltd
Category: otc | Type: HUMAN OTC DRUG LABEL
Date: 20200709

ACTIVE INGREDIENTS: CHLOROXYLENOL 0.3 g/100 g
INACTIVE INGREDIENTS: ALPHA-TOCOPHEROL ACETATE; METHYLPROPANEDIOL; CARBOMER 934; WATER; METHYL BENZOATE; ALOE; CAMELLIA SINENSIS SEED; TROLAMINE; POLYOXYL 40 HYDROGENATED CASTOR OIL; ROSEMARY

RINSE-FREE HAND SANITIZER GEL

Active Ingredient(s)

CHLOROXYLENOL 0 3%

Purpose

Antiseptic, Hand Sanitizer

Uses

For daily hand sanitizing

Warnings

For rexternal use, do not inhale or ingest

Keep out of reach of children.

WHEN USING

Avoid contact with broken skin and keep out of eyes. In case of contact with eyes, flush thoroughly with water.

STORAGE AND HANDLING

Store below 43 C. Avoid lights and preserve in cool, dry and ventilated places.

STOP USE

Please test on a small area of skin before use, and stop use if skin irritation develops

Shall not apply as sanitizing for metalware

Directions

Open the cap and gently squeeze product into palm of hands, then rub thoroughly over all surfaces of both hands

Inactive ingredients

AQUA. METHYLPROPANEDIOL, CARBOMER,

PEG-40 HYDROGENATED CASTOR OIL. PARFUM,

TRIETHANOLAMINE ,ALOE BARBADENSIS LEAF EXTRACT,
CAMELLIA SINENSIS EXTRACT,
ROSMARINUS OFFICINALIS (ROSEMARY) LEAF EXTRACT,
TOCOPHERO